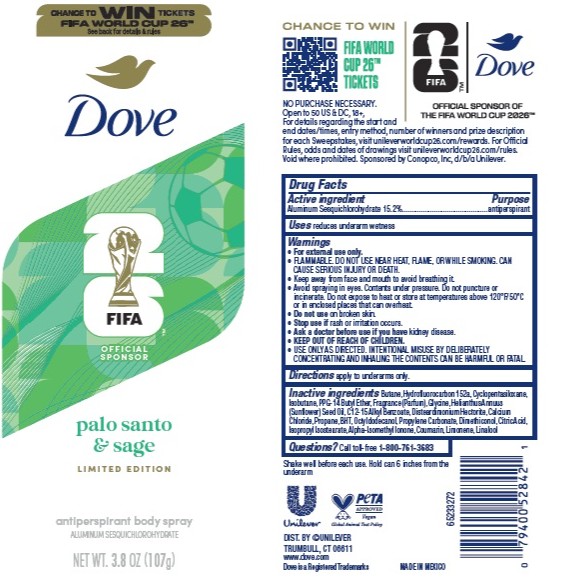 DRUG LABEL: Dove
NDC: 64942-2405 | Form: SPRAY
Manufacturer: Conopco d/b/a Unilever
Category: otc | Type: HUMAN OTC DRUG LABEL
Date: 20251201

ACTIVE INGREDIENTS: ALUMINUM SESQUICHLOROHYDRATE 15.2 g/100 g
INACTIVE INGREDIENTS: CALCIUM CHLORIDE; HYDROFLUOROCARBON 152A; HELIANTHUS ANNUUS (SUNFLOWER) SEED OIL; BHT; DIMETHICONOL (40 CST); GLYCINE; C12-15 ALKYL BENZOATE; PROPANE; PROPYLENE CARBONATE; CITRIC ACID; BUTANE; CYCLOPENTASILOXANE; ALPHA-ISOMETHYL IONONE; ISOPROPYL ISOSTEARATE; COUMARIN; DISTEARDIMONIUM HECTORITE; LIMONENE, (+)-; LINALOOL; OCTYLDODECANOL; ISOBUTANE; PPG-14 BUTYL ETHER

Dove FIFA 26 Palo Santo and Sage Limited Edition Antiperspirant Body Spray

DESCRIPTION

Dove FIFA 26 Palo Santo and Sage Limited Edition Antiperspirant Body Spray

ACTIVE INGREDIENT

Aluminum Sesquichlorohydrate 15.2%

PURPOSE

Antiperspirant

INDICATIONS AND USAGE

reduces underarm wetness

WARNINGS

• For external use only.
• FLAMMABLE. DO NOT USE NEAR HEAT, FLAME, OR WHILE SMOKING. CAN CAUSE SERIOUS INJURY OR DEATH.
• Keep away from face and mouth to avoid breathing it.
• Avoid spraying in eyes. Contents under pressure. Do not puncture or incinerate. Do not expose to heat or store at temperatures above 120°F/50°C or in enclosed places that can overheat.
• Do not use on broken skin. • Stop use if rash or irritation occurs.• Ask a doctor before use if you have kidney disease. • USE ONLY AS DIRECTED. INTENTIONAL MISUSE BY DELIBERATELY CONCENTRATING AND INHALING THE CONTENTS CAN BE HARMFUL OR FATAL.

• KEEP OUT OF REACH OF CHILDREN.

DOSAGE AND ADMINISTRATION

apply to underarms only

INACTIVE INGREDIENT

Butane, Hydrofluorocarbon 152a, Cyclopentasiloxane,
Isobutane, PPG-14 Butyl Ether, Fragrance (Parfum), Glycine, Helianthus Annuus
(Sunflower) Seed Oil, C12-15 Alkyl Benzoate, Disteardimonium Hectorite, Calcium
Chloride, Propane, BHT, Octyldodecanol, Propylene Carbonate, Dimethiconol, Citric Acid,
Isopropyl Isostearate,Alpha-Isomethyl Ionone,Coumarin,Limonene, Linalool